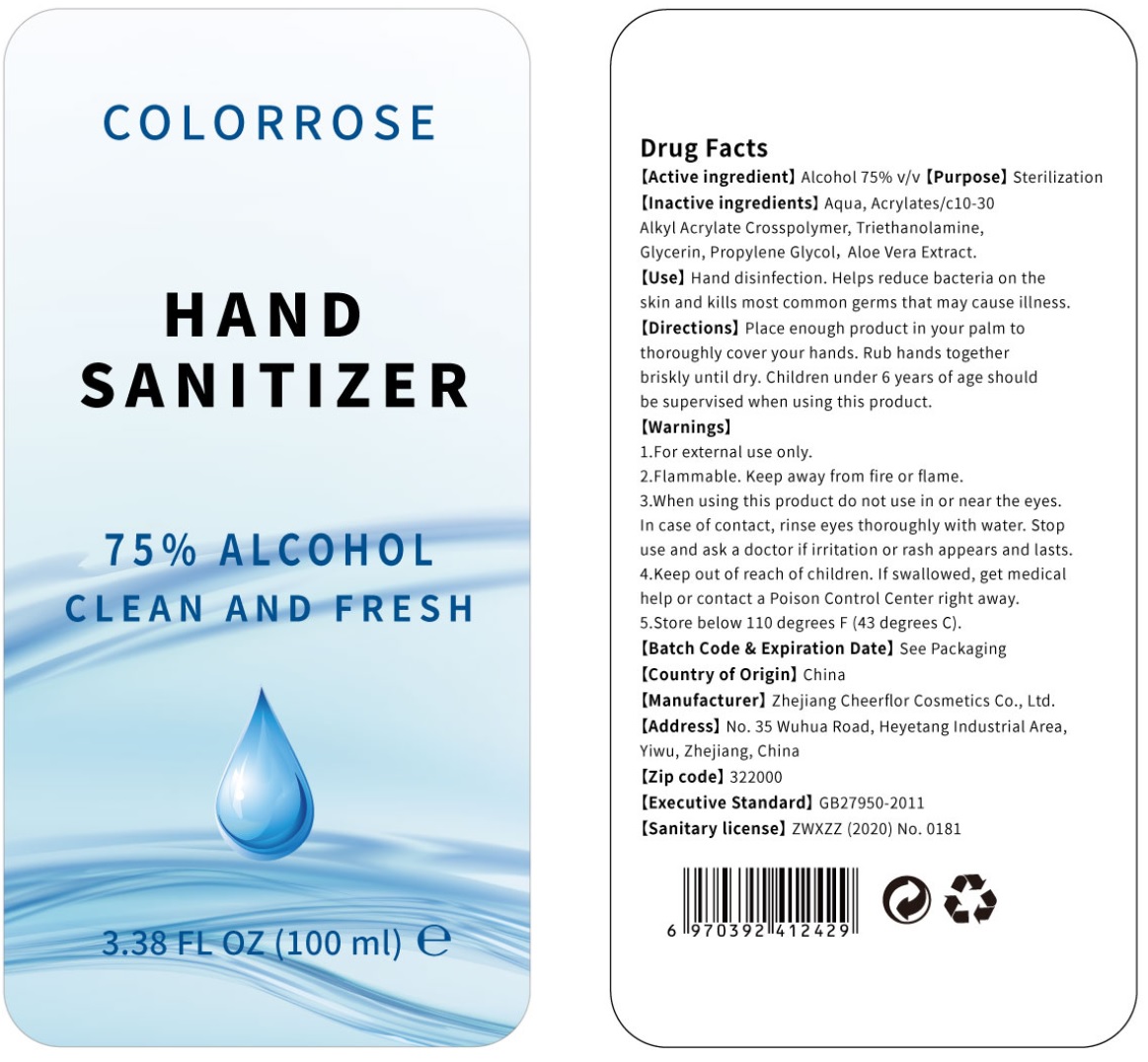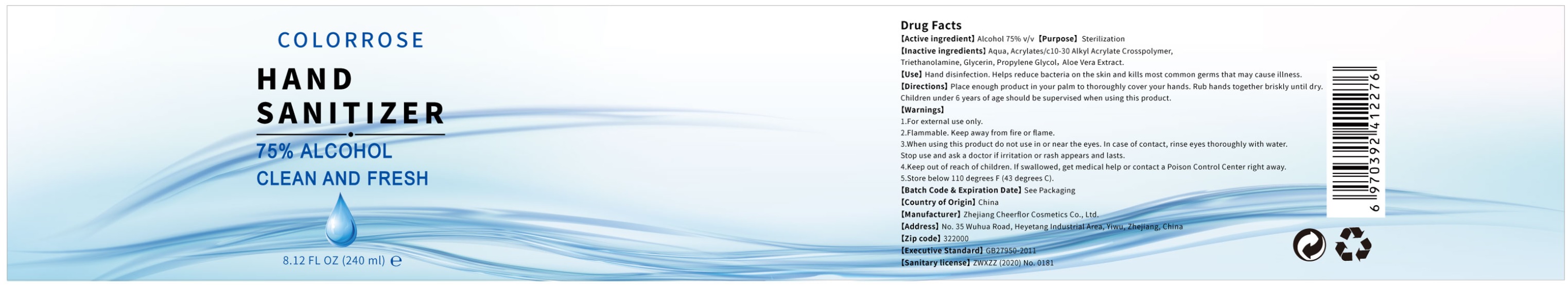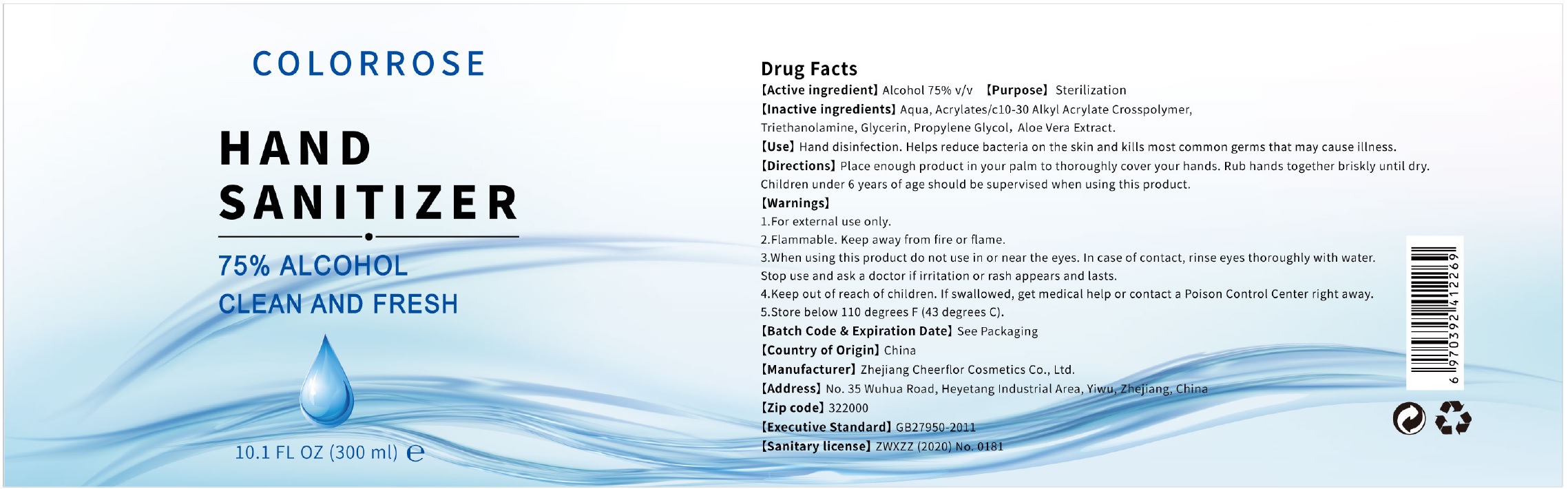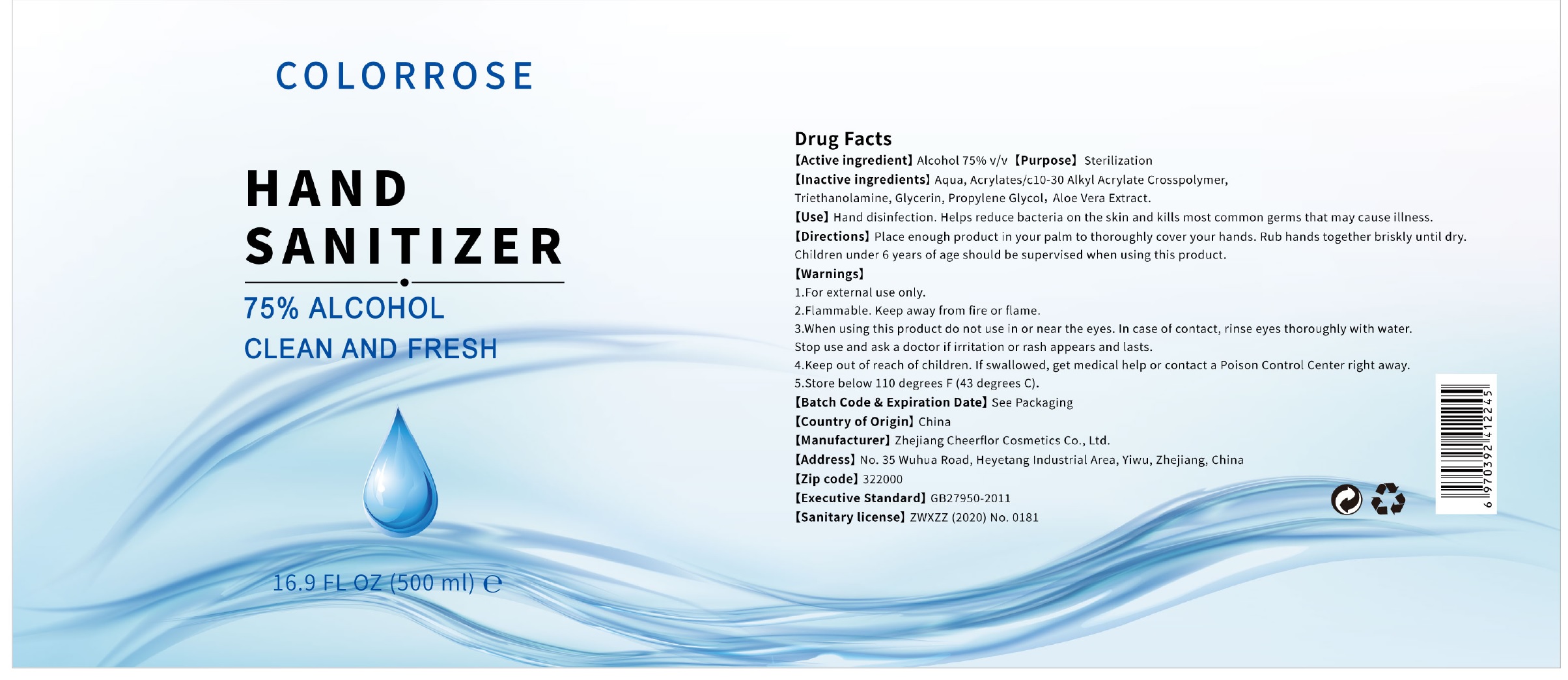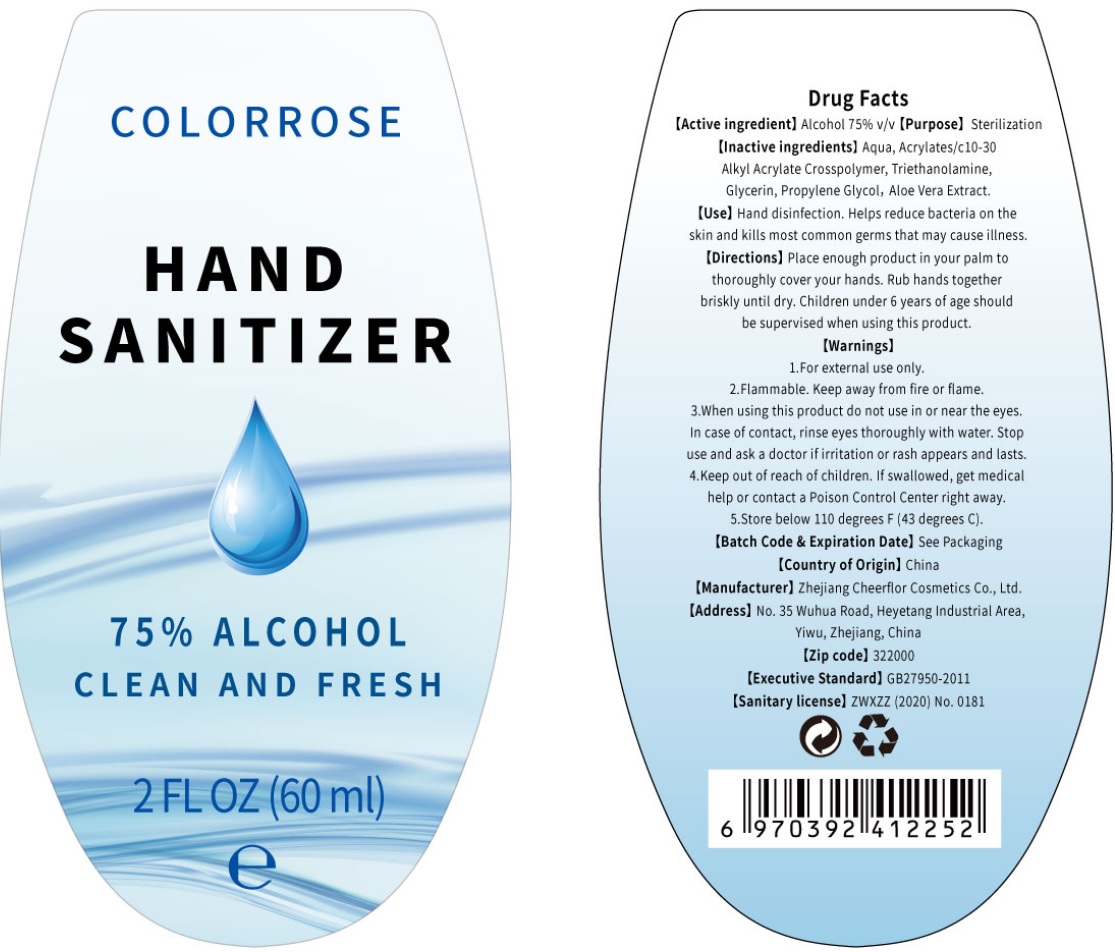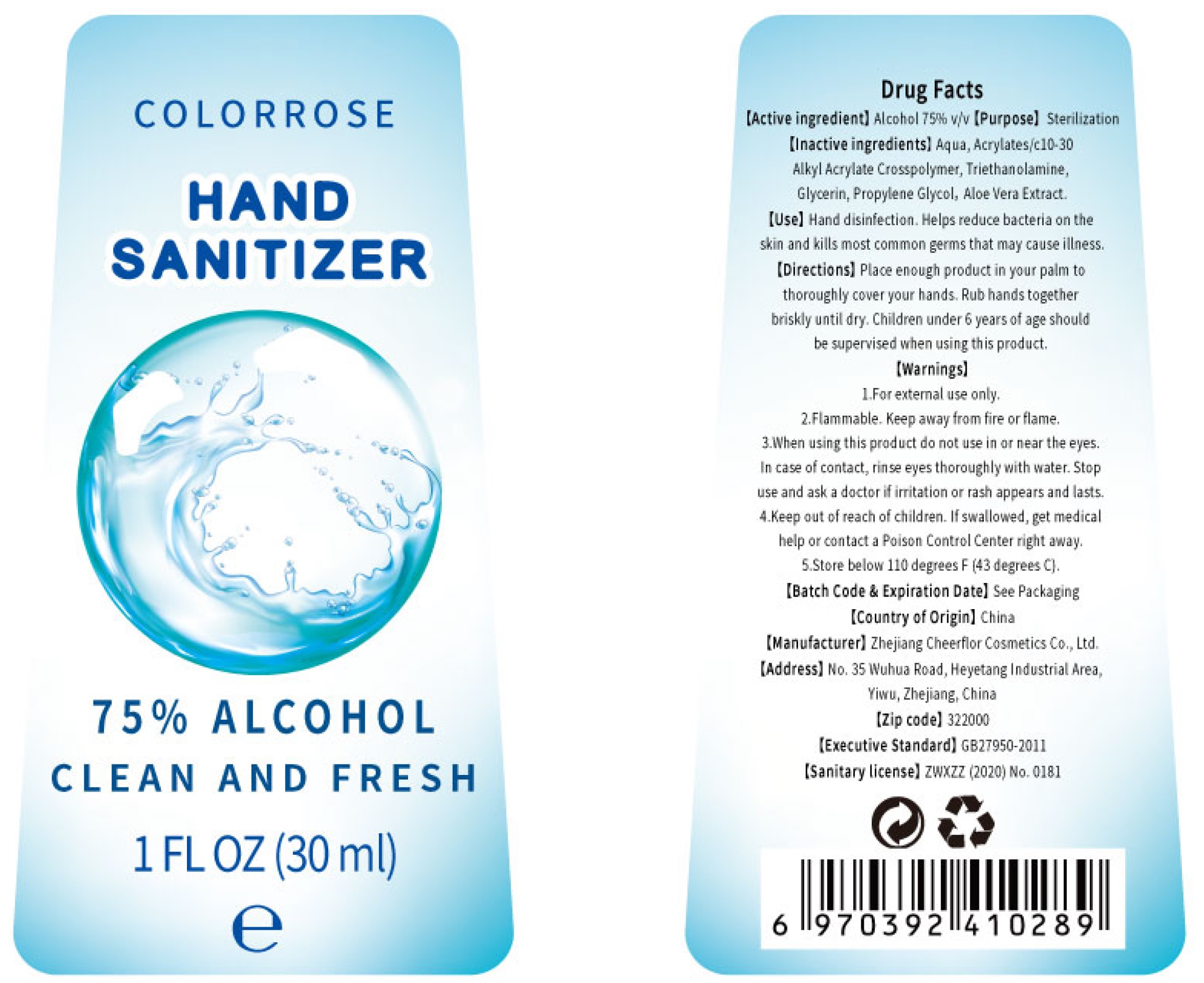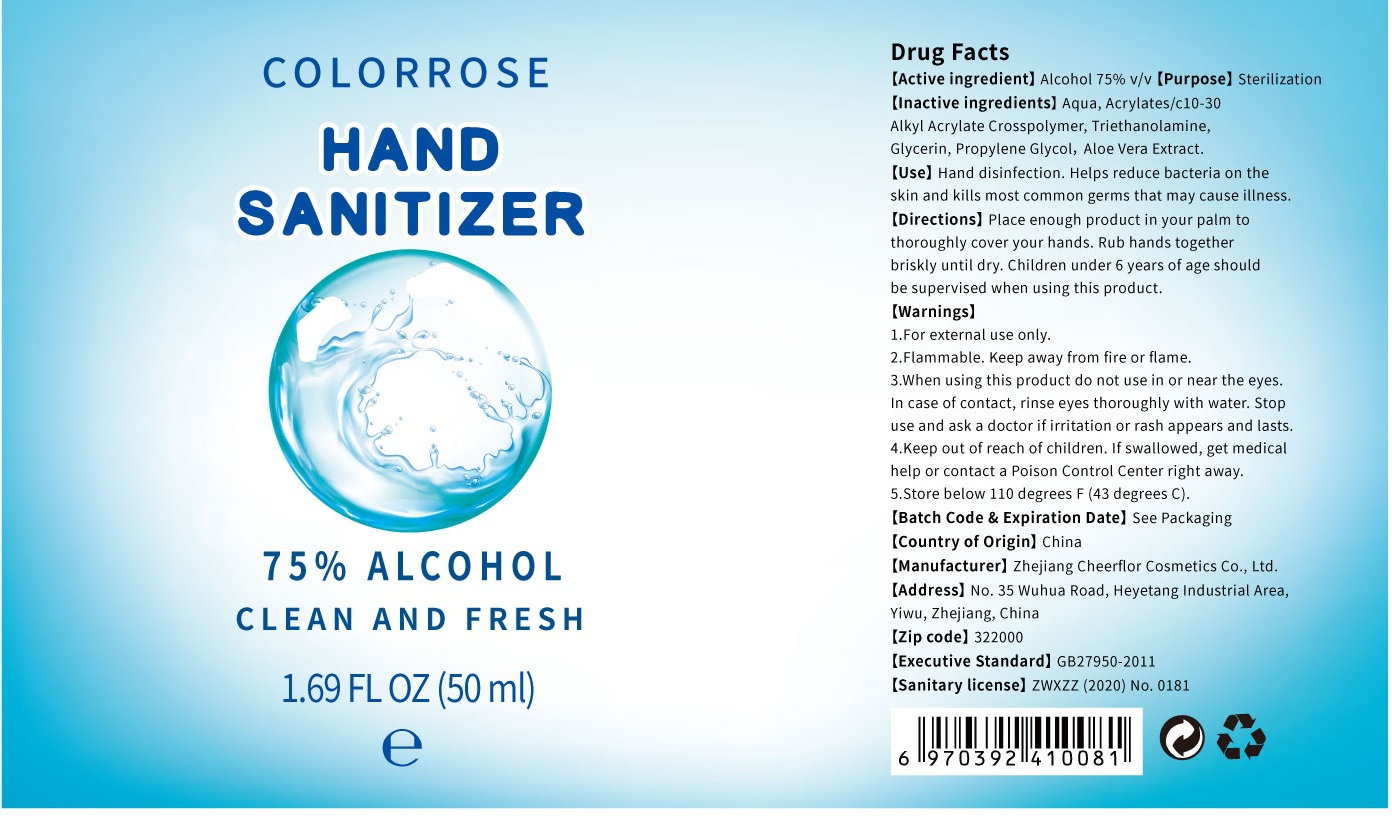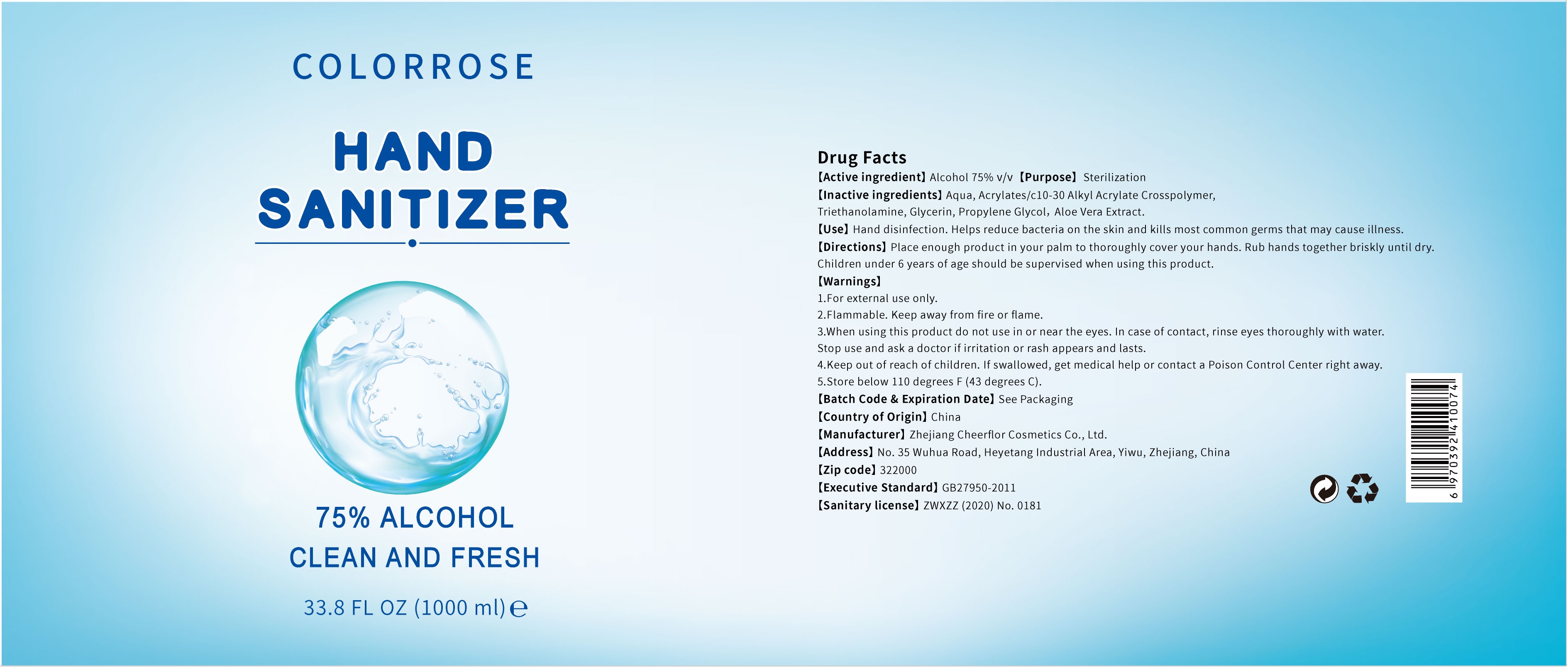 DRUG LABEL: Colorrose Hand Sanitizer
NDC: 78163-001 | Form: GEL
Manufacturer: Zhejiang Cheerflor Cosmetics Co., Ltd.
Category: otc | Type: HUMAN OTC DRUG LABEL
Date: 20200604

ACTIVE INGREDIENTS: ALCOHOL 0.75 mL/1 mL
INACTIVE INGREDIENTS: WATER; CARBOMER INTERPOLYMER TYPE A (ALLYL SUCROSE CROSSLINKED); TROLAMINE; GLYCERIN; PROPYLENE GLYCOL; ALOE VERA LEAF

Colorrose Hand Sanitizer

[Active ingredient]

Alcohol 75% v/v

[Purpose]

Sterilization

[Inactive ingredients]

Aqua, Acrylates/C10-30 alkyl Acrylate Crosspolymer, Triethanolamine, Glycerin, Propylene Glycol, Aloe Vera Extract.

[Use]

Hand disinfection. Helps reduce bacteria on the skin and kills most common germs that may cause illness.

[Directions]

Place enough product in your palm to thoroughly cover your hands. Rub hands together briskly until dry. Children under 6 years of age should be supervised when using this product.

[Warnings]

1. For external use only.
2. Flammable. Keep away from fire or flame.

3.When using this product

do not use in or near the eyes .In case of contact, rinse eyes thoroughly with water.

Stop use and ask a doctor

if irritation on rash appears and lasts.

4.Keep out of reach of children.

If swallowed, get medical help or contact a Poison Control Center right away.

5.Store below 110 degrees F [43 degrees C].